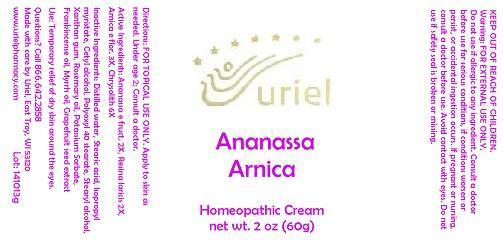 DRUG LABEL: Ananassa Arnica
NDC: 48951-1265 | Form: CREAM
Manufacturer: Uriel Pharmacy Inc.
Category: homeopathic | Type: HUMAN OTC DRUG LABEL
Date: 20150130

ACTIVE INGREDIENTS: PINEAPPLE 2 [hp_X]/1 g; LARIX DECIDUA RESIN 2 [hp_X]/1 g; ARNICA MONTANA FLOWER 2 [hp_X]/1 g; COLLOIDAL SILICON DIOXIDE 6 [hp_X]/1 g
INACTIVE INGREDIENTS: WATER; STEARIC ACID; ISOPROPYL MYRISTATE; CETYL ALCOHOL; POLYOXYL 40 STEARATE; STEARYL ALCOHOL; XANTHAN GUM; ROSEMARY OIL; POTASSIUM SORBATE; FRANKINCENSE OIL; MYRRH OIL; CITRUS PARADISI SEED

Ananassa Arnica

INDICATIONS AND USAGE

Directions: FOR TOPICAL USE ONLY.

DOSAGE AND ADMINISTRATION

Apply to skin as needed. Under age 2: Consult a doctor.

ACTIVE INGREDIENT

Active Ingredients: Ananassa e fruct. 2X, Resina laricis 2X, Arnica e flor. 3X, Chrysolith 6X

INACTIVE INGREDIENT

Inactive Ingredients: Distilled water, Stearic acid, Isopropyl myristate, Cetyl alcohol, Polyoxyl 40 stearate, Stearyl alcohol, Xanthan gum, Rosemary oil, Potassium Sorbate, Frankincense oil, Myrrh oil, Grapefruit seed extract

PURPOSE

Use: Temporary relief of dry skin around the eyes.

KEEP OUT OF REACH OF CHILDREN.

WARNINGS

Warning: FOR EXTERNAL USE ONLY.
Do not use if allergic to any ingredient. Consult a doctor before use for serious conditions, if conditions worsen or persist, or accidental ingestion occurs. If pregnant or nursing, consult a doctor before use. Avoid contact with eyes. Do not use if safety seal is broken or missing.

Questions? Call 866.642.2858
Made with care by Uriel, East Troy, WI 53120
www.urielpharmacy.com